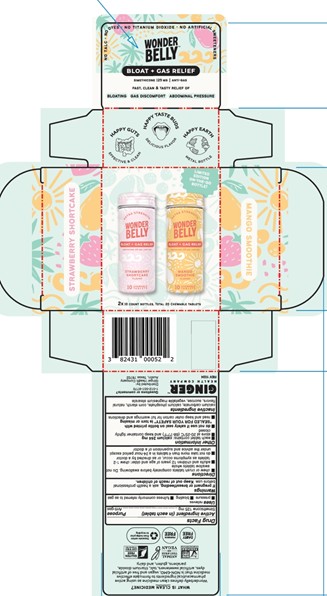 DRUG LABEL: Wonderbelly Extra Strength Anti-Gas
NDC: 82431-291 | Form: KIT | Route: ORAL
Manufacturer: Ginger Health Company
Category: otc | Type: HUMAN OTC DRUG LABEL
Date: 20251027

ACTIVE INGREDIENTS: DIMETHICONE 125 mg/1 1; DIMETHICONE 125 mg/1 1
INACTIVE INGREDIENTS: DIBASIC CALCIUM PHOSPHATE DIHYDRATE; CALCIUM CARBONATE; TRIBASIC CALCIUM PHOSPHATE; STARCH, CORN; MAGNESIUM STEARATE; SUCROSE; DIBASIC CALCIUM PHOSPHATE DIHYDRATE; SUCROSE; TRIBASIC CALCIUM PHOSPHATE; MAGNESIUM STEARATE; CALCIUM CARBONATE; STARCH, CORN

Strawberry Shortcake + Mango Smoothie Bloat+Gas Kit

Drug Facts

Active ingredient (in each tablet)

Simethicone 125 mg

Purpose

Anti-gas

Uses

relieves

- pressure
- bloating
- fullness commonly referred to as gas

Warnings

If pregnant or breastfeeding,

ask a health professional before use

Directions

- chew or crush tablets completely before swallowing. Do not swallow tablets whole.
- adults and children 12 years of age and older: chew 1-2 tablets as symptoms occur, or as directed by a doctor
- do not take more than 4 tablets in a 24-hour period except under the advice and supervision of a doctor

Other information

- each tablet contains: calcium 218 mg
- store at 20-25°C (68-77°F) and keep container tightly closed
- do not use if safety seal on bottle printed with "SEALED FOR YOUR SAFETY" is torn or missing
- read and keep outer carton for full warnings and directions

Inactive ingredients

calcium carbonate, calcium phosphate, corn starch, natural flavors, sucrose, vegetable magnesium stearate

Questions or comments?

call 1-512-551-9770

Distributed by:

Ginger Health Company

Austin, Texas 78702

Principal Display Panel

No Talc, No Dyes, No Titanium Dioxide, No Artificial Sweeteners

WONDERBELLY

BLOAT + GAS RELIEF

Simethicone 125 mg | Anti-gas

Fast, Clean, and Tasty Relief of

Bloating

Gas Discomfort

Abdominal Pressure

2x10 Count Bottles, Total 20 Chewable Tablets